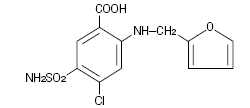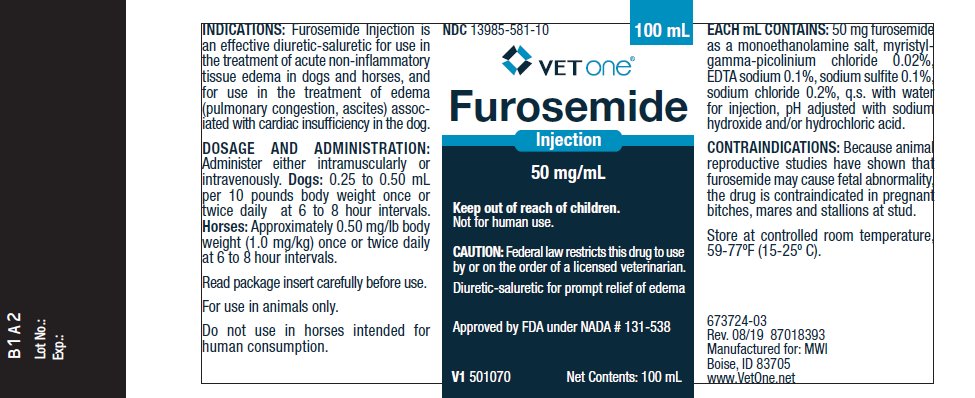 DRUG LABEL: Furosemide
NDC: 13985-581 | Form: INJECTION
Manufacturer: MWI/VetOne
Category: animal | Type: PRESCRIPTION ANIMAL DRUG LABEL
Date: 20250428

ACTIVE INGREDIENTS: FUROSEMIDE 50 mg/1 mL
INACTIVE INGREDIENTS: MIRIPIRIUM CHLORIDE 0.2 mg/1 mL; EDETATE DISODIUM 1 mg/1 mL; SODIUM SULFITE 1 mg/1 mL; SODIUM CHLORIDE 2 mg/1 mL; 2-AMINOETHANOL 10 mg/1 mL; WATER

Furosemide Injection
50 mg/mL

Approved by FDA under NADA # 131-538

Caution:

Federal law restricts this drug to use by or on the order of a licensed veterinarian.

Description:

Furosemide is a potent loop diuretic which is a derivative of anthranilic acid. The structure is:

Chemical Name: 4-Chloro-N-furfuryl-5-sulfamoylanthranilic acid. Furosemide is pharmacodynamically characterized by the following.

1) Administered intramuscularly, it begins to act in about 30 minutes, and diuretic response is produced. When administered intravenously, the response is in about 5 minutes. ^(1 2)

2) Is a loop diuretic which inhibits reabsorption of sodium and chloride at the ascending loop of Henle in the kidneys, enhancing water excretion. ^3

3) A dose-response relationship and a ratio of minimum to maximum effective dose range greater than tenfold. ^1

4) A high degree of efficacy, low inherent toxicity and a high therapeutic index.

DESCRIPTION

Each mL contains: 50 mg furosemide as a monoethanolamine salt, myristyl-gamma-picolinium chloride 0.02%, EDTA sodium 0.1%, sodium sulfite 0.1% with sodium chloride 0.2% in water for injection, pH adjusted with sodium hydroxide and/or hydrochloric acid.

Actions:

The therapeutic efficacy of Furosemide Injection is from the activity of the intact and unaltered molecule throughout the nephron, inhibiting the reabsorption of sodium not only in the proximal and distal tubule but also in the ascending limb of the loop of Henle. The prompt onset of action is a result of the drug’s rapid absorption and a poor lipid solubility. The low lipid solubility and a rapid renal excretion minimize the possibility of its accumulation in tissues and organs or crystalluria. Furosemide has no inhibitory effect on carbonic anhydrase or aldosterone activity in the distal tubule. The drug possesses diuretic activity either in the presence of acidosis or alkalosis. ^(1 3 4 5 6)

Indications:

Dogs and Horses: Furosemide Injection is an effective diuretic-saluretic for use in the treatment of acute noninflammatory tissue edema in dogs and horses, and for use in the treatment of edema (pulmonary congestion, ascites) associated with cardiac insufficiency in the dog.

In cases of edema involving cardiac insufficiency, the continued use of heart stimulants such as digitalis or its glycosides is indicated.

The rationale for efficacious use of diuretic therapy in either dogs or horses is determined by the clinical pathology producing the edema.

Dosage and Administration:

Dogs—Administer intravenously or intramuscularly 0.25 to 0.50 mL per 10 pounds body weight once or twice daily at 6 to 8 hour intervals.

The dosage should be adjusted to the individual’s response. In severe edematous or refractory cases, the dose may be doubled or increased by increments of 1.0 mg per pound of body weight.

The established effective dose should be administered once or twice daily.

Discontinue diuretic therapy with Furosemide Injection, 50 mg/mL after initiation of acute fluid mobilization or stabilization of patient; when necessary Furosemide Tablets may be used for maintenance therapy (see Furosemide Tablets insert for details). Do not exceed treatment with Furosemide Injection, 50 mg/mL for more than 3 days. The daily schedule of administration can be timed to control the period of micturition for the convenience of the client or veterinarian.

Mobilization of the edema may be most efficiently and safely accomplished by utilizing an intermittent daily dose schedule, i.e., every other day or 2 to 4 consecutive days weekly.

Horses—The usual parenteral dosage of furosemide in horses is approximately 0.5 mg/lb body weight (1.0 mg/kg). See dosage schedule below. A prompt diuresis usually ensues from the initial treatment. Administer once or twice daily at 6 to 8 hour intervals either intravenously or intramuscularly until desired results are achieved.

The dosage should be adjusted to the individual’s response. In severe edematous or refractory cases, the dose may be doubled or increased by increments of 0.5 mg per pound of body weight.

The established effective dose should be administered once or twice daily. The daily schedule of administration can be timed to control the period of micturition for the convenience of the client or veterinarian.

Mobilization of the edema may be most efficiently and safely accomplished by utilizing an intermittent daily dose schedule, i.e., every other day or 2 to 4 consecutive days weekly.

Recommended Dosage Schedule:

Horses: Administer IV or IM once or twice daily at 6-8 hour intervals until desired results are achieved.

Body Weight (lbs) | Furosemide Inj.; (50 mg/mL)
500 | 4.6 mL
600 | 5.5 mL
700 | 6.4 mL
800 | 7.3 mL
900 | 8.2 mL
1000 | 9.1 mL
1100 | 10.0 mL
1200 | 10.9 mL

Diuretic therapy for both dogs and horses should be discontinued after reduction of the edema, or maintained after determining a carefully programmed dosage schedule to prevent recurrence of edema. For long-term treatment, the dose can generally be lowered after the edema has once been reduced. Re-examination and consultations with the client will enhance the establishment of a satisfactorily programmed dosage schedule. Clinical examination and serum BUN, CO2 and electrolyte determinations should be performed during the early period of therapy and periodically thereafter, especially in refractory cases. Abnormalities should be corrected or the drug temporarily withdrawn.

Contraindications:

Animal reproductive studies have shown that furosemide may cause fetal abnormality and the drug is contraindicated in pregnant bitches, mares and stallions at stud.

Furosemide is contraindicated in anuria, furosemide hypersensitivity, hepatic coma, or during electrolytic imbalances. Monitor serum electrolytes, BUN and CO2 frequently. Monitor serum potassium levels and watch for signs of hypocalcemia.

Corticosteroids cause an additive potassium-depletion effect.

Warnings:

Furosemide Injection is a highly effective diuretic and, if given in excessive amounts, as with any diuretic, may lead to excessive diuresis which could result in electrolyte imbalance, dehydration and reduction of plasma volume, enhancing the risk of circulatory collapse, thrombosis and embolism. Therefore, the animal should be observed for early signs of fluid depletion with electrolyte imbalance, and corrective measures administered. Excessive loss of potassium in patients receiving digitalis or its glycosides may precipitate digitalis toxicity.

Caution should be exercised in animals administered potassium-depleting steroids. Correct potassium deficiency with proper dietary supplementation. If animal needs potassium supplements, use oral liquid form; do not use enteric-coated potassium tablets.

The concurrent use of furosemide with some antibiotics may be inadvisable. There is evidence that the drug enhances the nephrotoxic potential of aminoglycosides, cephalosporins and polymyxins and increases the ototoxic effects of all aminoglycosides.

Sulfonamide diuretics have been reported to decrease arterial responsiveness to pressor amines and to enhance the effect of tubocurarine.

Caution should be exercised in administering curare or its derivatives to patients undergoing therapy with Furosemide Injection and it is advisable to discontinue Furosemide Injection for one day prior to any elective surgery.

Do not use in horses intended for human consumption.

Precautions:

Furosemide Injection is a highly effective diuretic-saluretic which, if given in excessive amounts, may result in dehydration and have to be adjusted to the patient’s needs. The animal should be observed for early signs of electrolyte imbalance, and corrective measures administered. Early signs of electrolyte imbalance are increased thirst, lethargy, drowsiness or restlessness, fatigue, oliguria, gastro-intestinal disturbances and tachycardia.

Special attention should be given to potassium levels.

Furosemide Injection may lower serum calcium levels and cause tetany in rare cases of animals having an existing hypocalcemic tendency. ^(7 8 9 10 11)

Furosemide Injection is contraindicated in anuria. Therapy should be discontinued in cases of progressive renal disease if increasing azotemia and oliguria occur during the treatment. Sudden alterations of fluid and electrolyte imbalance in an animal with cirrhosis may precipitate hepatic coma, therefore, observation during period of therapy is necessary. In hepatic coma and in states of electrolyte depletion, therapy should not be instituted until the basic condition is improved or corrected.

Potassium supplementation may be necessary in cases routinely treated with potassium-depleting steroids.

Active or latent diabetes mellitis may on rare occasions be exacerbated by furosemide. Transient loss of auditory capacity has been experimentally produced in cats following intravenous injections of excessive doses of furosemide at a very rapid rate. ^(12 13 14)

Animal Safety:

Furosemide demonstrates a very low order of either acute or chronic toxicity. The drug is rapidly absorbed and excreted by both glomerular filtration and tubular secretion. The rates of excretion are of such magnitude that cumulation of furosemide does not occur despite repeated administrations. ^15

The main effect observed in clinical toxicity is an abnormality of fluid and electrolyte imbalances. Ototoxicity resulting in transient loss of hearing has been reported with furosemide. ^15

A safety study was performed in dogs to determine the effects of Furosemide Injection at increasing dosages and time elements. The dosage levels were 1.5 mg/lb body weight (recommended dosage), 4.5 mg/lb body weight (3X recommended dosage) and 7.5 mg/lb body weight (5X recommended dosage). The treatment period ranged up to nine days in length. Results demonstrate very slight tubular nephrosis at the higher dosage levels.

In addition, serum levels of potassium and chloride were slightly lowered in the higher dosage groups. Cumulative evaluation of the data demonstrates that Furosemide Injection is safe when administered at the recommended dosage for a duration of nine consecutive days.

To report suspected adverse reactions, to obtain a Safety Data Sheet or for technical assistance, call 1-888-637-4251. For additional information about adverse drug experience reporting for animal drugs, contact FDA at 1-888-FDA-VETS, or www.fda.gov/reportanimalae.

Storage:

Store at controlled room temperature between 59°–77°F (15°–25°C). When used as labeled, there is no limit on the number of punctures throughout the full expiry period.

How Supplied:

Furosemide Injection, 50 mg/mL is supplied in 100 mL multi-dose vials.

NDC 13985-581-10 – 100 mL

References:

1. Timmerman, R.J., F.R. Springman and R.K. Thoms, 1964. Evaluation of Furosemide, a New Diuretic Agent. Current Therapeutic Research, 6(2): 88-94.

2. Martindale, The Extra Pharmacopoeia, 27th ed., 1977. The Pharmaceutical Press, London, 556.

3. Suki, W., F.C. Rector, Jr. and D.W. Seldin, 1965. The Site of Action of Furosemide and Other Sulfonamide Diuretics in the Dog. Journal of Clinical Investigation, 44(9):1458-1469.

4. Berman, L.B. and A. Ebrahimi, 1965. Experiences with Furosemide in Renal Disease. Proc. Society for Experimental Biological Medicine, 118:333-336.

5. Schmidt, H.A.E. Animal Experiments with S35 Tagged Lasix® in Canine and Ovine. Radio-chemical Pharmacological Laboratory, Farbwerke Hoechst, Frankfurt, West Germany.

6. Haussler, A. and P. Hajdu. Methods Biological Identification and Results of Studies on Absorption, Elimination and Metabolism. Research Laboratories, Farbwerke Hoechst, Frankfurt, West Germany.

7. Antoniou, L.D., G.M. Eisner, L.M. Slotkoff and L.S. Lilienfield, 1967. Sodium and Calcium Transport in the Kidney. Clinical Research, 15(2):476.

8. Duarte, C.G., 1967. Effects of Furosemide (F) and Ethacrynic Acid (ETA) on the Renal Clearance of Phosphate (Cp), Ultrafilterable Calcium (CUfCa) and Magnesium (CUfMg). Clinical Research, 15(2):357.

9. Duarte, C.G., 1968. Effects of Ethacrynic Acid and Furosemide on Urinary Calcium, Phosphate and Magnesium. Metabolism, 17:867-876.

10. Nielsen, S.P., O. Andersen and K.E. Steven, 1969. Magnesium and Calcium Metabolism during Prolonged Furosemide (Lasix®) Administration to Normal Rats. Acta Pharmacol. et. Toxicol., 27:469-479.

11. Reimold, E.W., 1972. The Effect of Furosemide on Hypercalcemia Due to Dihydrotachysterol. Metabolism, 21(7): 593-598.

12. Brown, R.D., and T.W. McElwee, Jr., 1972. Effects of Intra-Arterially and Intravenously Administered Ethacrynic Acid and Furosemide on Cochlear N1 in Cats. Toxicology and Applied Pharmacology, 22:589-594.

13. Mathog, R.H., W.G. Thomas and W.R. Hudson, 1970. Ototoxicity of New and Potent Diuretics. Archives of Otolaryngology, 92(1):7-13.

14. Mathog, R.H. and G.J. Matz, 1972. Ototoxic Effects of Ethacrynic Acid. Annals of Otolaryngology, Vol. 81.

15. Gilman, A.G., L.S. Goodman and A. Gilman, 1980. The Pharmacological Basis of Therapeutics, Sixth ed., MacMillan Publishing Co., Inc., New York, NY, 903-907.

673724-03

Rev. 08/19 87018393

Manufactured for: MWI

Boise, ID 83705

www.VetOne.net

Principal Display Panel – 100 mL Container Label

NDC 13985-581-10

Furosemide

Injection

50 mg/mL

Keep out of reach of children.

Not for human use.

CAUTION: Federal law restricts this drug to use by or on the order of a licensed veterinarian.

Diuretic-saluretic for prompt relief of edema

Approved by FDA under NADA #131-538

V1 501070

Net Contents: 100 mL